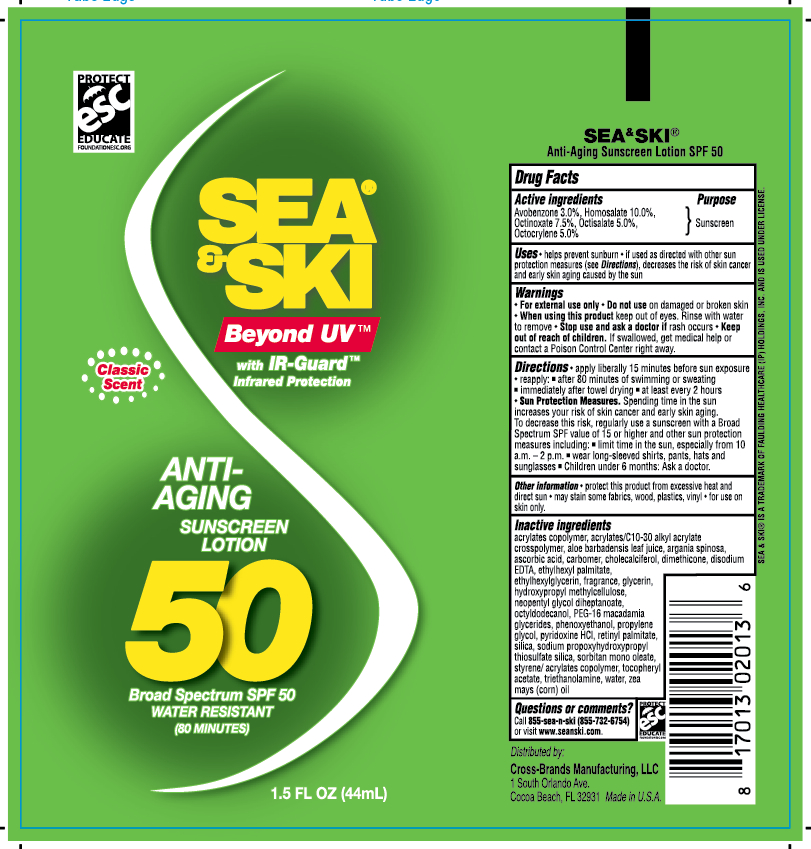 DRUG LABEL: General Protection
NDC: 71153-2013 | Form: LOTION
Manufacturer: Cross-Brands Manufacturing LLC
Category: otc | Type: HUMAN OTC DRUG LABEL
Date: 20170226

ACTIVE INGREDIENTS: HOMOSALATE 10 g/1 mL; OCTINOXATE 7.5 g/1 mL; OCTISALATE 5 g/1 mL; OCTOCRYLENE 5 g/1 mL; AVOBENZONE 3 g/1 mL
INACTIVE INGREDIENTS: ALOE VERA LEAF; GLYCERIN

Sea & Ski SPF 50 Tube